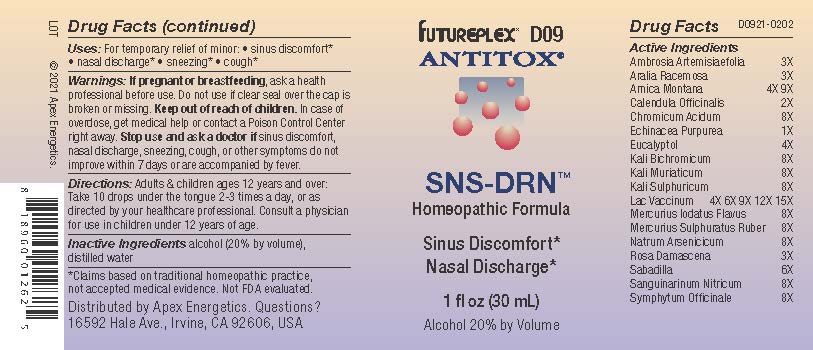 DRUG LABEL: D09
NDC: 63479-0409 | Form: SOLUTION/ DROPS
Manufacturer: Apex Energetics Inc.
Category: homeopathic | Type: HUMAN OTC DRUG LABEL
Date: 20240108

ACTIVE INGREDIENTS: COMFREY ROOT 8 [hp_X]/1 mL; POTASSIUM CHLORIDE 8 [hp_X]/1 mL; POTASSIUM SULFATE 8 [hp_X]/1 mL; MERCURIC SULFIDE 8 [hp_X]/1 mL; SODIUM ARSENATE, DIBASIC, HEPTAHYDRATE 8 [hp_X]/1 mL; ROSA DAMASCENA FLOWERING TOP 3 [hp_X]/1 mL; CALENDULA OFFICINALIS FLOWERING TOP 2 [hp_X]/1 mL; ECHINACEA PURPUREA 1 [hp_X]/1 mL; SCHOENOCAULON OFFICINALE SEED 6 [hp_X]/1 mL; AMBROSIA ARTEMISIIFOLIA 3 [hp_X]/1 mL; ARALIA RACEMOSA ROOT 3 [hp_X]/1 mL; EUCALYPTOL 4 [hp_X]/1 mL; COW MILK 15 [hp_X]/1 mL; SANGUINARINE NITRATE 8 [hp_X]/1 mL; CHROMIUM TRIOXIDE 8 [hp_X]/1 mL; POTASSIUM DICHROMATE 8 [hp_X]/1 mL; MERCUROUS IODIDE 8 [hp_X]/1 mL; ARNICA MONTANA 9 [hp_X]/1 mL
INACTIVE INGREDIENTS: WATER; ALCOHOL

D09

Active Ingredients
Ambrosia Artemisiaefolia | 3X
Aralia Racemosa | 3X
Arnica Montana | 4X 9X
Calendula Officinalis | 2X
Chromicum Acidum | 8X
Echinacea Purpurea | 1X
Eucalyptol | 4X
Kali Bichromicum | 8X
Kali Muriaticum | 8X
Kali Sulphuricum | 8X
Lac Vaccinum | 4X 6X 9X 12X 15X
Mercurius Iodatus Flavus | 8X
Mercurius Sulphuratus Ruber | 8X
Natrum Arsenicicum | 8X
Rosa Damascena | 3X
Sabadilla | 6X
Sanguinarinum Nitricum | 8X
Symphytum Officinale | 8X

INDICATIONS AND USAGE

Uses:

For temporary relief of minor:

sinus discomfort*

nasal discharge*

sneezing*

cough*

*Claims based on traditional homeopathic practice, not accepted medical evidence. Not FDA evaluated.

Warnings:

PREGNANCY OR BREAST FEEDING

If pregnant or breastfeeding, ask a health professional before use.

Do not use if clear seal over the cap is broken or missing.

Keep out of reach of children. In case of overdose, get medical help or contact a Poison Control Center right away.

Stop use and ask a doctor if sinus discomfort, nasal discharge, sneezing, cough, or other symptoms do not improve within 7 days or are accompanied by fever.

Directions:

Adults & children ages 12 years and over: Take 10 drops under the tongue 2-3 times a day, or as directed by your healthcare professional. Consult a physician for use in children under 12 years of age.

Inactive Ingredients

alcohol (20% by volume), distilled water

Distributed by Apex Energetics. Questions?

16592 Hale Ave., Irvine, CA 92606, USA

PACKAGE LABEL

FUTUREPLEX® D09

ANTITOX®

SNS-DRN™

Homeopathic Formula

Sinus Discomfort*

Nasal Discharge*

1 fl oz (30 mL)

Alcohol 20% by Volume